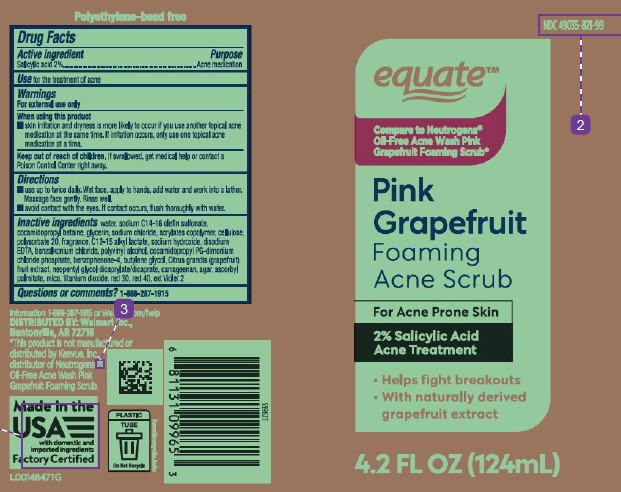 DRUG LABEL: Acne Scrub
NDC: 49035-821 | Form: GEL
Manufacturer: Walmart Inc.
Category: otc | Type: HUMAN OTC DRUG LABEL
Date: 20260227

ACTIVE INGREDIENTS: SALICYLIC ACID 20 mg/1 mL
INACTIVE INGREDIENTS: COCAMIDOPROPYL BETAINE; GLYCERIN; SODIUM CHLORIDE; BUTYL ACRYLATE/METHYL METHACRYLATE/METHACRYLIC ACID COPOLYMER (18000 MW); POWDERED CELLULOSE; POLYSORBATE 20; C12-15 ALKYL LACTATE; SODIUM HYDROXIDE; EDETATE DISODIUM; BENZALKONIUM CHLORIDE; POLYVINYL ALCOHOL, UNSPECIFIED; COCAMIDOPROPYL PROPYLENE GLYCOL-DIMONIUM CHLORIDE PHOSPHATE; SULISOBENZONE; BUTYLENE GLYCOL; PUMMELO; NEOPENTYL GLYCOL DICAPRYLATE/DICAPRATE; CARRAGEENAN; AGAR; ASCORBYL PALMITATE; MICA; TITANIUM DIOXIDE; D&C RED NO. 30; FD&C RED NO. 40; D&C VIOLET NO. 2; WATER; SODIUM C14-16 OLEFIN SULFONATE

Equate 821.004/821AH-AI
Acne Scrub Pink Grapefruit

CLAIM

Polyethylene-bead free

active ingredient

Salicylic acid 2%

Purpose

Acne Medication

use

For the treatment of acne

Warnings

For external use only

When using this product

- skin irritation and dryness is more likely to occur if you use another topical acne medication at the same time. If irritation occurs, only use one topical acne medication at a time.

Keep out of reach of children.

If swallowed, get medical help or contact a Poison Control Center right away.

Directions

- use up to twice daily. Wet face, apply to hands, add water and work into a lather. Massage face gently. Rinse well.
- avoid contact with the eyes. If contact occurs, flush thoroughly with water.

Inactive ingredients

water, sodium C14-16 olefin sulfonate, cocamidopropyl betaine, glycerin, sodium chloride, acrylates copolymer, cellulose, polysorbate 20, fragrance, C12-15 alkyl lactate, sodium hydroxide, disodium EDTA, benzalkonium chloride, polyvinyl alcohol, cocamidopropyl PG-dimonium chloride phosphate, benzophenone-4, butylene glycol, Citrus grandis (grapefruit) fruit extract, neopentyl glycol dicaprylate/dicaprate, carrageenan, agar, ascorbyl palmitate, mica, titanium dioxide, red 30, red 40, ext Violet 2

Questions or comments?

1-888-287-1915

Adverse reactions

Information: 1-888-287-1915 or Walmart.com/help

Distributed by: Walmart Inc.,

Bentonville, AR 72716

Made in the USA with domestic and imported ingredients

Factory Certified

PLASTIC TUBE

Do Not Recycle

how2recycle.info

Dislaimer

*This product is not manufactured or distributed by Kenvue, Inc., distributor of Neutrogena®Oil-Free Acne Oil-Free Acne Wash Pink Grapefruit Foaming Scrub.

principal display panel

NDC 49035-821-99

equate™

Compare to Neutrogena®Oil-Free Acne Wash Pink Grapefruit Foaming Scrub*

PINK GRAPEFRUIT

FOAMING ACNE SCRUB

For Acne Prone Skin

2% Salicylic Acid Acne Treatment

- Helps fight breakouts
- With naturally derived grapefruit extract

4.2 FL OZ (124 mL)